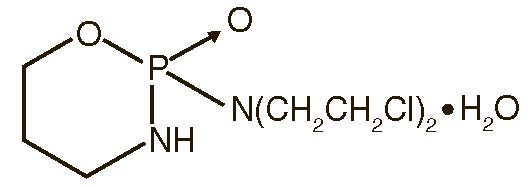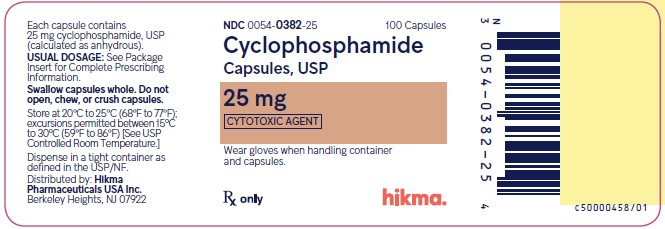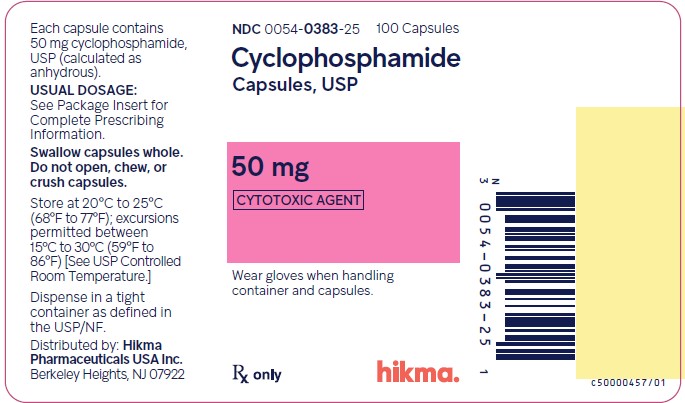 DRUG LABEL: Cyclophosphamide
NDC: 0054-0382 | Form: CAPSULE
Manufacturer: Hikma Pharmaceuticals USA Inc.
Category: prescription | Type: HUMAN PRESCRIPTION DRUG LABEL
Date: 20241119

ACTIVE INGREDIENTS: CYCLOPHOSPHAMIDE 25 mg/1 1
INACTIVE INGREDIENTS: STARCH, CORN; SODIUM STEARYL FUMARATE; FD&C BLUE NO. 1; GELATIN, UNSPECIFIED; FD&C RED NO. 40; AMMONIA; TITANIUM DIOXIDE; FERROSOFERRIC OXIDE; ISOPROPYL ALCOHOL; BUTYL ALCOHOL; PROPYLENE GLYCOL; SHELLAC

HIGHLIGHTS OF PRESCRIBING INFORMATION

These highlights do not include all the information needed to use Cyclophosphamide Capsules safely and effectively. See full prescribing information for Cyclophosphamide Capsules.
Cyclophosphamide capsules, for oral use
Initial U.S. Approval: 1959

1 INDICATIONS AND USAGE

Cyclophosphamide is an alkylating drug indicated for treatment of:

- Malignant Diseases: malignant lymphomas: Hodgkin’s disease, lymphocytic lymphoma, mixed-cell type lymphoma, histiocytic lymphoma, Burkitt’s lymphoma; multiple myeloma, leukemias, mycosis fungoides, neuroblastoma, adenocarcinoma of ovary, retinoblastoma, breast carcinoma (1.1)
- Minimal Change Nephrotic Syndrome in Pediatric Patients: biopsy proven minimal change nephrotic syndrome in pediatric patients who failed to adequately respond to or are unable to tolerate adrenocorticosteroid therapy (1.2)

Limitations of Use:

The safety and effectiveness for the treatment of nephrotic syndrome in adults or other renal disease has not been established.

2 DOSAGE AND ADMINISTRATION

During or immediately after the administration, administer adequate amounts of fluid to reduce the risk of urinary tract toxicity (2.1).

Malignant Diseases: Adult and Pediatric Patients (2.2)

- Oral: Usually 1 mg per kg per day to 5 mg per kg orally once daily for both initial and maintenance dosing.

Minimal Change Nephrotic Syndrome in Pediatric Patients (2.3)

- Recommended oral dose: 2 mg per kg once daily for 8 to 12 weeks (maximum cumulative dose 168 mg per kg). Treatment beyond 90 days increases the probability of sterility in males.

3 DOSAGE FORMS AND STRENGTHS

Capsules: 25 mg and 50 mg (3)

4 CONTRAINDICATIONS

- Hypersensitivity to cyclophosphamide (4)
- Urinary outflow obstruction (4)

5 WARNINGS AND PRECAUTIONS

- Myelosuppression, Immunosuppression, Bone Marrow Failure and Infections – Severe immunosuppression may lead to serious and sometimes fatal infections. Close hematological monitoring is required. (5.1)
- Urinary Tract and Renal Toxicity – Hemorrhagic cystitis, pyelitis, ureteritis, and hematuria can occur. Exclude or correct any urinary tract obstructions prior to treatment. (5.2)
- Cardiotoxicity – Myocarditis, myopericarditis, pericardial effusion, arrythmias and congestive heart failure, which may be fatal, have been reported. Monitor patients, especially those with risk factors for cardiotoxicity or pre-existing cardiac disease. (5.3)
- Pulmonary Toxicity – Pneumonitis, pulmonary fibrosis and pulmonary veno-occlusive disease leading to respiratory failure may occur. Monitor patients for signs and symptoms of pulmonary toxicity. (5.4)
- Secondary malignancies (5.5)
- Veno-occlusive Liver Disease - Fatal outcome can occur. (5.6)
- Embryo-Fetal Toxicity - Can cause fetal harm. Advise patients of potential risk to the fetus and to use effective contraception. (5.7, 8.1, 8.3)

6 ADVERSE REACTIONS

Adverse reactions reported most often include neutropenia, febrile neutropenia, fever, alopecia, nausea, vomiting, and diarrhea. (6.1)

To report SUSPECTED ADVERSE REACTIONS, contact Hikma Pharmaceuticals USA Inc. at 1-800-962-8364 or FDA at 1-800-FDA-1088 or www.fda.gov/medwatch.

8 USE IN SPECIFIC POPULATIONS

- Lactation: Advise not to breastfeed. (8.2)
- Females and Males of Reproductive Potential: Verify pregnancy status prior to initiation of Cyclophosphamide Capsules. May impair fertility. (8.3)
- Renal Impairment: Monitor for toxicity in patients with moderate and severe renal impairment. (8.6, 12.3)

FULL PRESCRIBING INFORMATION

1 INDICATIONS AND USAGE

1.1 Malignant Diseases

Cyclophosphamide Capsules are indicated for the treatment of:

- malignant lymphomas (Stages III and IV of the Ann Arbor staging system), Hodgkin’s disease, lymphocytic lymphoma (nodular or diffuse), mixed-cell type lymphoma, histiocytic lymphoma, Burkitt’s lymphoma
- multiple myeloma
- leukemias: chronic lymphocytic leukemia, chronic granulocytic leukemia (it is usually ineffective in acute blastic crisis), acute myelogenous and monocytic leukemia, acute lymphoblastic (stem-cell) leukemia (cyclophosphamide given during remission is effective in prolonging its duration)
- mycosis fungoides (advanced disease)
- neuroblastoma (disseminated disease)
- adenocarcinoma of the ovary
- retinoblastoma
- carcinoma of the breast

Cyclophosphamide Capsules, although effective alone in susceptible malignancies, is more frequently used concurrently or sequentially with other antineoplastic drugs.

1.2 Minimal Change Nephrotic Syndrome in Pediatric Patients

Cyclophosphamide Capsules are indicated for the treatment of biopsy proven minimal change nephrotic syndrome in pediatric patients who failed to adequately respond to or are unable to tolerate adrenocorticosteroid therapy.

Limitations of Use:
The safety and effectiveness of Cyclophosphamide Capsules for the treatment of nephrotic syndrome in adults or other renal disease has not been established.

2 DOSAGE AND ADMINISTRATION

2.1 Hydration and Important Administration Instructions

During or immediately after the administration of Cyclophosphamide Capsules, adequate amounts of fluid should be ingested or infused to force diuresis in order to reduce the risk of urinary tract toxicity. Therefore, Cyclophosphamide Capsules should be taken in the morning.

Cyclophosphamide Capsules should be swallowed whole. The capsules should not be opened, chewed, or crushed.

Cyclophosphamide Capsules is a cytotoxic drug. Follow applicable special handling and disposal procedures.^1 Exposure to broken capsules should be avoided. If contact with broken capsules occurs, wash hands immediately and thoroughly.

2.2 Recommended Dosage for Malignant Diseases

Adults and Pediatric Patients

The recommended dosage of Cyclophosphamide Capsules is in the range of 1 mg per kg to 5 mg per kg orally once daily for both initial and maintenance dosing.

Other regimens of intravenous and oral cyclophosphamide have been reported. Dosages should be adjusted based on evidence of antitumor activity, myelosuppression, or other severe adverse reactions [see Warnings and Precautions (5)].

When cyclophosphamide is included in combined cytotoxic regimens, it may be necessary to reduce the dose of cyclophosphamide, as well as that of the other drugs.

2.3 Recommended Dosage for Minimal Change Nephrotic Syndrome in Pediatric Patients

The recommended dosage of Cyclophosphamide Capsules is 2 mg per kg orally once daily for 8 to 12 weeks (maximum cumulative dose 168 mg per kg). Treatment beyond 90 days increases the probability of sterility in males [see Use in Specific Populations (8.4)].

3 DOSAGE FORMS AND STRENGTHS

Capsules:

- 25 mg capsule for oral administration contains 25 mg of cyclophosphamide, USP. It is a blue/blue opaque capsule with “54 006” printed in black ink on the cap and body, containing a white to off-white powder.
- 50 mg capsule for oral administration contains 50 mg of cyclophosphamide, USP. It is a blue/blue opaque capsule with “54 881” printed in black ink on the cap and body, containing a white to off-white powder.

4 CONTRAINDICATIONS

Cyclophosphamide Capsules are contraindicated in patients with:

- A history of severe hypersensitivity reactions to cyclophosphamide, any of its metabolites, or to other components of the product. Anaphylactic reactions including death have been reported with cyclophosphamide. Cross-sensitivity with other alkylating agents can occur.
- In patients with urinary outflow obstruction [see Warnings and Precautions (5.2)].

5 WARNINGS AND PRECAUTIONS

5.1 Myelosuppression, Immunosuppression, Bone Marrow Failure and Infections

Cyclophosphamide can cause myelosuppression (leukopenia, neutropenia, thrombocytopenia and anemia), bone marrow failure, and severe immunosuppression which may lead to serious and sometimes fatal infections, including sepsis and septic shock. Latent infections can be reactivated [see Adverse Reactions (6.2)].

Antimicrobial prophylaxis may be indicated in certain cases of neutropenia at the discretion of the managing physician. In case of neutropenic fever, antibiotic therapy is indicated. Antimycotics and/or antivirals may also be indicated.

Monitoring of complete blood counts is essential during cyclophosphamide treatment so that the dose can be adjusted, if needed. Cyclophosphamide should not be administered to patients with neutrophils ≤1,500/mm^3 and platelets <50,000/mm^3. Cyclophosphamide treatment may not be indicated, or should be interrupted, or the dose reduced, in patients who have or who develop a serious infection. G-CSF may be administered to reduce the risks of neutropenia complications associated with cyclophosphamide use. Primary and secondary prophylaxis with G-CSF should be considered in all patients considered to be at increased risk for neutropenia complications. The nadirs of the reduction in leukocyte count and thrombocyte count are usually reached in weeks 1 and 2 of treatment. Peripheral blood cell counts are expected to normalize after approximately 20 days. Bone marrow failure has been reported. Severe myelosuppression may be expected particularly in patients pretreated with and/or receiving concomitant chemotherapy and/or radiation therapy.

5.2 Urinary Tract and Renal Toxicity

Hemorrhagic cystitis, pyelitis, ureteritis, and hematuria have been reported with cyclophosphamide. Medical and/or surgical supportive treatment may be required to treat protracted cases of severe hemorrhagic cystitis. Discontinue cyclophosphamide therapy in case of severe hemorrhagic cystitis.

Urotoxicity (bladder ulceration, necrosis, fibrosis, contracture and secondary cancer) may require interruption of cyclophosphamide treatment or cystectomy. Urotoxicity can be fatal. Urotoxicity can occur with short-term or long-term use of cyclophosphamide.

Before starting treatment, exclude or correct any urinary tract obstructions [see Contraindications (4)]. Urinary sediment should be checked regularly for the presence of erythrocytes and other signs of urotoxicity and/or nephrotoxicity. Cyclophosphamide should be used with caution, if at all, in patients with active urinary tract infections. Aggressive hydration with forced diuresis and frequent bladder emptying can reduce the frequency and severity of bladder toxicity. Mesna has been used to prevent severe bladder toxicity.

5.3 Cardiotoxicity

Myocarditis, myopericarditis, pericardial effusion including cardiac tamponade, and congestive heart failure, which may be fatal, have been reported with cyclophosphamide therapy.

Supraventricular arrhythmias (including atrial fibrillation and flutter) and ventricular arrhythmias (including severe QT prolongation associated with ventricular tachyarrhythmia) have been reported after treatment with regimens that included cyclophosphamide.

The risk of cardiotoxicity may be increased with high doses of cyclophosphamide, in patients with advanced age, and in patients with previous radiation treatment to the cardiac region and/or previous or concomitant treatment with other cardiotoxic agents.

Particular caution is necessary in patients with risk factors for cardiotoxicity and in patients with pre-existing cardiac disease.

Monitor patients with risk factors for cardiotoxicity and with pre-existing cardiac disease.

5.4 Pulmonary Toxicity

Pneumonitis, pulmonary fibrosis, pulmonary veno-occlusive disease and other forms of pulmonary toxicity leading to respiratory failure have been reported during and following treatment with cyclophosphamide. Late onset pneumonitis (greater than 6 months after start of cyclophosphamide) appears to be associated with increased mortality. Pneumonitis may develop years after treatment with cyclophosphamide.

Monitor patients for signs and symptoms of pulmonary toxicity.

5.5 Secondary Malignancies

Cyclophosphamide is genotoxic [see Nonclinical Toxicology (13.1)]. Secondary malignancies (urinary tract cancer, myelodysplasia, acute leukemias, lymphomas, thyroid cancer, and sarcomas) have been reported in patients treated with cyclophosphamide-containing regimens. The risk of bladder cancer may be reduced by prevention of hemorrhagic cystitis.

5.6 Veno-occlusive Liver Disease

Veno-occlusive liver disease (VOD) including fatal outcome has been reported in patients receiving cyclophosphamide-containing regimens. A cytoreductive regimen in preparation for bone marrow transplantation that consists of cyclophosphamide in combination with whole-body irradiation, busulfan, or other agents has been identified as a major risk factor. VOD has also been reported to develop gradually in patients receiving long-term low-dose immunosuppressive doses of cyclophosphamide. Other risk factors predisposing to the development of VOD include preexisting disturbances of hepatic function, previous radiation therapy of the abdomen, and a low performance status.

5.7 Embryo-Fetal Toxicity

Based on its mechanism of action and published reports of effects in pregnant patients or animals, Cyclophosphamide Capsules can cause fetal harm when administered to a pregnant woman [see Use in Specific Populations (8.1), Clinical Pharmacology (12.1) and Nonclinical Toxicology (13.1)]. Exposure to cyclophosphamide during pregnancy may cause birth defects, miscarriage, fetal growth retardation, and fetotoxic effects in the newborn. Cyclophosphamide is teratogenic and embryo-fetal toxic in mice, rats, rabbits and monkeys.

Advise pregnant women and female patients of reproductive potential of the potential risk to the fetus [see Use in Specific Populations (8.1)]. Verify the pregnancy status of females of reproductive potential prior to initiation of Cyclophosphamide Capsules. Advise females of reproductive potential to use effective contraception during treatment with Cyclophosphamide Capsules and for up to 1 year after completion of therapy. Advise male patients with female partners of reproductive potential to use effective contraception during treatment with Cyclophosphamide Capsules and for 4 months after completion of therapy [see Use in Specific Populations (8.1, 8.3)].

5.8 Infertility

Male and female reproductive function and fertility may be impaired in patients being treated with Cyclophosphamide Capsules. Cyclophosphamide interferes with oogenesis and spermatogenesis. It may cause sterility in both sexes. Development of sterility appears to depend on the dose of cyclophosphamide, duration of therapy, and the state of gonadal function at the time of treatment. Cyclophosphamide-induced sterility may be irreversible in some patients. Advise patients on the potential risks for infertility [see Use in Specific Populations (8.3) and (8.4)].

5.9 Impairment of Wound Healing

Cyclophosphamide may interfere with normal wound healing.

5.10 Hyponatremia

Hyponatremia associated with increased total body water, acute water intoxication, and a syndrome resembling SIADH (syndrome of inappropriate secretion of antidiuretic hormone), which may be fatal, has been reported.

6 ADVERSE REACTIONS

The following adverse reactions are discussed in more detail in other sections of the labeling.

- Hypersensitivity [see Contraindications (4)]
- Myelosuppression, Immunosuppression, Bone Marrow Failure, and Infections [see Warnings and Precautions (5.1)]
- Urinary Tract and Renal Toxicity [see Warnings and Precautions (5.2)]
- Cardiotoxicity [see Warnings and Precautions (5.3)]
- Pulmonary Toxicity [see Warnings and Precautions (5.4)]
- Secondary Malignancies [see Warnings and Precautions (5.5)]
- Veno-occlusive Liver Disease [see Warnings and Precautions (5.6)]
- Infertility [see Warnings and Precautions (5.8) and Use in Specific Populations (8.3) and (8.4)]
- Impaired Wound Healing [see Warnings and Precautions (5.9)]
- Hyponatremia [see Warnings and Precautions (5.10)]

6.1 Common Adverse Reactions

Hematopoietic system

Neutropenia occurs in patients treated with cyclophosphamide. The degree of neutropenia is particularly important because it correlates with a reduction in resistance to infections. Fever without documented infection has been reported in neutropenic patients.

Gastrointestinal system

Nausea and vomiting occur with cyclophosphamide therapy. Anorexia and, less frequently, abdominal discomfort or pain and diarrhea may occur. There are isolated reports of hemorrhagic colitis, oral mucosal ulceration and jaundice occurring during therapy.

Skin and its structures

Alopecia occurs in patients treated with cyclophosphamide. Skin rash occurs occasionally in patients receiving the drug. Pigmentation of the skin and changes in nails can occur.

6.2 Postmarketing Experience

The following adverse reactions have been identified from clinical trials or post-marketing surveillance. Because they are reported from a population from unknown size, precise estimates of frequency cannot be made.

Cardiac: cardiac arrest, ventricular fibrillation, ventricular tachycardia, cardiogenic shock, pericardial effusion (progressing to cardiac tamponade), myocardial hemorrhage, myocardial infarction, cardiac failure (including fatal outcomes), cardiomyopathy, myocarditis, pericarditis, carditis, atrial fibrillation, supraventricular arrhythmia, ventricular arrhythmia, bradycardia, tachycardia, palpitations, QT prolongation.

Congenital, Familial and Genetic: intra-uterine death, fetal malformation, fetal growth retardation, fetal toxicity (including myelosuppression, gastroenteritis).

Ear and Labyrinth: deafness, hearing impaired, tinnitus.

Endocrine: water intoxication.

Eye: visual impairment, conjunctivitis, lacrimation.

Gastrointestinal: gastrointestinal hemorrhage, acute pancreatitis, colitis, enteritis, cecitis, stomatitis, constipation, parotid gland inflammation.

General Disorders and Administrative Site Conditions: multiorgan failure, general physical deterioration, influenza-like illness, pyrexia, edema, chest pain, mucosal inflammation, asthenia, pain, chills, fatigue, malaise, headache.

Hematologic: myelosuppression, bone marrow failure, disseminated intravascular coagulation and hemolytic uremic syndrome (with thrombotic microangiopathy).

Hepatic: veno-occlusive liver disease, cholestatic hepatitis, cytolytic hepatitis, hepatitis, cholestasis; hepatotoxicity with hepatic failure, hepatic encephalopathy, ascites, hepatomegaly, blood bilirubin increased, hepatic function abnormal, hepatic enzymes increased.

Immune: immunosuppression, anaphylactic shock and hypersensitivity reaction.

Infections: The following manifestations have been associated with myelosuppression and immunosuppression caused by cyclophosphamide: increased risk for and severity of pneumonias (including fatal outcomes), other bacterial, fungal, viral, protozoal and, parasitic infections; reactivation of latent infections, (including viral hepatitis, tuberculosis), Pneumocystis jiroveci, herpes zoster, Strongyloides, sepsis and septic shock.

Investigations: blood lactate dehydrogenase increased, C-reactive protein increased.

Metabolism and Nutrition: hyponatremia, fluid retention, blood glucose increased, blood glucose decreased.

Musculoskeletal and Connective Tissue: rhabdomyolysis, scleroderma, muscle spasms, myalgia, arthralgia.

Neoplasms: acute leukemia, myelodysplastic syndrome, lymphoma, sarcomas, renal cell carcinoma, renal pelvis cancer, bladder cancer, ureteric cancer, thyroid cancer.

Nervous System: encephalopathy, convulsion, dizziness, neurotoxicity has been reported and manifested as reversible posterior leukoencephalopathy syndrome, myelopathy, peripheral neuropathy, polyneuropathy, neuralgia, dysesthesia, hypoesthesia, paresthesia, tremor, dysgeusia, hypogeusia, parosmia.

Pregnancy: premature labor.

Psychiatric: confusional state.

Renal and Urinary: renal failure, renal tubular disorder, renal impairment, nephropathy toxic, hemorrhagic cystitis, bladder necrosis, cystitis ulcerative, bladder contracture, hematuria, nephrogenic diabetes insipidus, atypical urinary bladder epithelial cells.

Reproductive System: infertility, ovarian failure, ovarian disorder, amenorrhea, oligomenorrhea, testicular atrophy, azoospermia, oligospermia.

Respiratory: pulmonary veno-occlusive disease, acute respiratory distress syndrome, interstitial lung disease as manifested by respiratory failure (including fatal outcomes), obliterative bronchiolitis, organizing pneumonia, alveolitis allergic, pneumonitis, pulmonary hemorrhage; respiratory distress, pulmonary hypertension, pulmonary edema, pleural effusion, bronchospasm, dyspnea, hypoxia, cough, nasal congestion, nasal discomfort, oropharyngeal pain, rhinorrhea.

Skin and Subcutaneous Tissue: toxic epidermal necrolysis, Stevens-Johnson syndrome, erythema multiforme, palmar-plantar erythrodysesthesia syndrome, radiation recall dermatitis, toxic skin eruption, urticaria, dermatitis, blister, pruritus, erythema, nail disorder, facial swelling, hyperhidrosis.

Tumor Lysis Syndrome: like other cytotoxic drugs, cyclophosphamide may induce tumor-lysis syndrome and hyperuricemia in patients with rapidly growing tumors.

Vascular: pulmonary embolism, venous thrombosis, vasculitis, peripheral ischemia, hypertension, hypotension, flushing, hot flush.

7 DRUG INTERACTIONS

Cyclophosphamide is a pro-drug that is activated by cytochrome P450s [see Clinical Pharmacology (12.3)].

An increase of the concentration of cytotoxic metabolites may occur with:

- Protease inhibitors: Concomitant use of protease inhibitors may increase the concentration of cytotoxic metabolites. Use of protease inhibitor-based regimens was found to be associated with a higher incidence of infections and neutropenia in patients receiving cyclophosphamide, doxorubicin, and etoposide (CDE) than use of a Non-Nucleoside Reverse Transcriptase Inhibitor-based regimen.

Combined or sequential use of cyclophosphamide and other agents with similar toxicities can potentiate toxicities.

- Increased hematotoxicity and/or immunosuppression may result from a combined effect of cyclophosphamide and, for example:
  - ACE inhibitors: ACE inhibitors can cause leukopenia.
  - Natalizumab
  - Paclitaxel: Increased hematotoxicity has been reported when cyclophosphamide was administered after paclitaxel infusion.
  - Thiazide diuretics
  - Zidovudine
- Increased cardiotoxicity may result from a combined effect of cyclophosphamide and, for example:
  - Anthracyclines
- Cytarabine
- Pentostatin
- Radiation therapy of the cardiac region
- Trastuzumab
- Increased pulmonary toxicity may result from a combined effect of cyclophosphamide and, for example:
  - Amiodarone
  - G-CSF, GM-CSF (granulocyte colony-stimulating factor, granulocyte macrophage colony-stimulating factor): Reports suggest an increased risk of pulmonary toxicity in patients treated with cytotoxic chemotherapy that includes cyclophosphamide and G-CSF or GMCSF.
- Increased nephrotoxicity may result from a combined effect of cyclophosphamide and, for example:
  - Amphotericin B
  - Indomethacin: Acute water intoxication has been reported with concomitant use of indomethacin
- Increase in other toxicities:
  - Azathioprine: Increased risk of hepatotoxicity (liver necrosis)
  - Busulfan: Increased incidence of hepatic veno-occlusive disease and mucositis has been reported.
  - Protease inhibitors: Increased incidence of mucositis
- Increased risk of hemorrhagic cystitis may result from a combined effect of cyclophosphamide and past or concomitant radiation treatment.

Etanercept: In patients with Wegener’s granulomatosis, the addition of etanercept to standard treatment, including cyclophosphamide, was associated with a higher incidence of non-cutaneous malignant solid tumors.

Metronidazole: Acute encephalopathy has been reported in a patient receiving cyclophosphamide and metronidazole. Causal association is unclear. In an animal study, the combination of cyclophosphamide with metronidazole was associated with increased cyclophosphamide toxicity.

Tamoxifen: Concomitant use of tamoxifen and chemotherapy may increase the risk of thromboembolic complications.

Coumarins: Both increased and decreased warfarin effect have been reported in patients receiving warfarin and cyclophosphamide.

Cyclosporine: Lower serum concentrations of cyclosporine have been observed in patients receiving a combination of cyclophosphamide and cyclosporine than in patients receiving only cyclosporine. This interaction may result in an increased incidence of graft-versus-host disease.

Depolarizing muscle relaxants: Cyclophosphamide treatment causes a marked and persistent inhibition of cholinesterase activity. Prolonged apnea may occur with concurrent depolarizing muscle relaxants (e.g., succinylcholine). If a patient has been treated with cyclophosphamide within 10 days of general anesthesia, alert the anesthesiologist.

8 USE IN SPECIFIC POPULATIONS

8.1 Pregnancy

Risk Summary

Based on its mechanism of action and published reports of effects in pregnant patients or animals, Cyclophosphamide Capsules can cause fetal harm when administered to a pregnant woman [see Clinical Pharmacology (12.1) and Nonclinical Toxicology (13.1)]. Exposure to cyclophosphamide during pregnancy may cause fetal malformations, miscarriage, fetal growth retardation, and toxic effects in the newborn [see Data]. Cyclophosphamide is teratogenic and embryo-fetal toxic in mice, rats, rabbits and monkeys [see Data]. Advise pregnant women and females of reproductive potential of the potential risk to the fetus.

The estimated background risk of major birth defects and miscarriage for the indicated population is unknown. In the U.S. general population, the estimated background risk of major birth defects is 2%-4% and of miscarriage is 15%-20% of clinically recognized pregnancies.

Data

Human Data

Malformations of the skeleton, palate, limbs and eyes as well as miscarriage have been reported after exposure to cyclophosphamide in the first trimester. Fetal growth retardation and toxic effects manifesting in the newborn, including leukopenia, anemia, pancytopenia, severe bone marrow hypoplasia, and gastroenteritis have been reported after exposure to cyclophosphamide.

Animal Data

Administration of cyclophosphamide to pregnant mice, rats, rabbits and monkeys during the period of organogenesis at doses at or below the dose in patients based on body surface area resulted in various malformations, which included neural tube defects, limb and digit defects and other skeletal anomalies, cleft lip and palate, and reduced skeletal ossification.

8.2 Lactation

Risk Summary

Cyclophosphamide is present in breast milk. Neutropenia, thrombocytopenia, low hemoglobin, and diarrhea have been reported in infants breast fed by women treated with cyclophosphamide. Because of the potential for serious adverse reactions in a breastfed child from Cyclophosphamide Capsules, advise lactating women not to breastfeed during the treatment and for 1 week after the last dose.

8.3 Females and Males of Reproductive Potential

Pregnancy Testing

Verify the pregnancy status of females of reproductive potential prior to the initiation of Cyclophosphamide Capsules [see Use in Specific Populations (8.1)].

Contraception

Females

Cyclophosphamide Capsules can cause fetal harm. Advise females of reproductive potential to use effective contraception during treatment with Cyclophosphamide Capsules for up to 1 year after completion of therapy [see Use in Specific Populations (8.1)].

Males

Based on findings in genetic toxicity and animal reproduction studies, advise male patients with female partners of reproductive potential to use effective contraception during treatment with Cyclophosphamide Capsules and for 4 months after completion of therapy [see Use in Specific Populations (8.1) and Nonclinical Toxicology (13.1)].

Infertility

Females

Amenorrhea, transient or permanent, associated with decreased estrogen and increased gonadotropin secretion develops in a proportion of women treated with cyclophosphamide. Affected patients generally resume regular menses within a few months after cessation of therapy. The risk of premature menopause with cyclophosphamide increases with age. Oligomenorrhea has also been reported in association with cyclophosphamide treatment.

Animal data suggest an increased risk of failed pregnancy and malformations may persist after discontinuation of cyclophosphamide as long as oocytes/follicles exist that were exposed to cyclophosphamide during any of their maturation phases. The exact duration of follicular development in humans is not known, but may be longer than 12 months [see Nonclinical Toxicology (13.1)].

Males

Men treated with cyclophosphamide may develop oligospermia or azoospermia which are normally associated with increased gonadotropin but normal testosterone secretion.

8.4 Pediatric Use

Pre-pubescent girls treated with cyclophosphamide generally develop secondary sexual characteristics normally and have regular menses. Ovarian fibrosis with apparently complete loss of germ cells after prolonged cyclophosphamide treatment in late pre-pubescence has been reported. Girls treated with cyclophosphamide who have retained ovarian function after completing treatment are at increased risk of developing premature menopause.

Pre-pubescent boys treated with cyclophosphamide develop secondary sexual characteristics normally, but may have oligospermia or azoospermia and increased gonadotropin secretion. Some degree of testicular atrophy may occur. Cyclophosphamide-induced azoospermia is reversible in some patients, though the reversibility may not occur for several years after cessation of therapy.

8.5 Geriatric Use

There is insufficient data from clinical studies of cyclophosphamide available for patients 65 years of age and older to determine whether they respond differently than younger patients. In general, dose selection for an elderly patient should be cautious, usually starting at the low end of the dosing range, reflecting the greater frequency of decreased hepatic, renal, or cardiac functioning, and of concomitant disease or other drug therapy.

8.6 Use in Patients with Renal Impairment

In patients with severe renal impairment, decreased renal excretion may result in increased plasma levels of cyclophosphamide and its metabolites. This may result in increased toxicity [see Clinical Pharmacology (12.3)]. Monitor patients with severe renal impairment (CrCl =10 mL/min to 24 mL/min) for signs and symptoms of toxicity.

Cyclophosphamide and its metabolites are dialyzable although there are probably quantitative differences depending upon the dialysis system being used. In patients requiring dialysis, use of a consistent interval between cyclophosphamide administration and dialysis should be considered.

8.7 Use in Patients with Hepatic Impairment

Patients with severe hepatic impairment have reduced conversion of cyclophosphamide to the active 4-hydroxyl metabolite, potentially reducing efficacy [see Clinical Pharmacology (12.3)].

10 OVERDOSAGE

No specific antidote for cyclophosphamide is known.

Overdosage should be managed with supportive measures, including appropriate treatment for any concurrent infection, myelosuppression, or cardiac toxicity should it occur.

Serious consequences of overdosage include manifestations of dose dependent toxicities such as myelosuppression, urotoxicity, cardiotoxicity (including cardiac failure), veno-occlusive hepatic disease, and stomatitis [see Warnings and Precautions (5.1, 5.2, 5.3, and 5.6)].

Patients who received an overdose should be closely monitored for the development of toxicities, and hematologic toxicity in particular.

Cyclophosphamide and its metabolites are dialyzable. Therefore, rapid hemodialysis is indicated when treating any suicidal or accidental overdose or intoxication.

Cystitis prophylaxis with mesna may be helpful in preventing or limiting urotoxic effects with cyclophosphamide overdose.

11 DESCRIPTION

Cyclophosphamide is a synthetic antineoplastic drug chemically related to the nitrogen mustards. The chemical name for cyclophosphamide is 2-[bis(2-chloroethyl)amino]tetrahydro-2H-1,3,2-oxazaphosphorine 2-oxide monohydrate, and has the following structural formula:

Cyclophosphamide has a molecular formula C7H15Cl2N2O2P • H2O and a molecular weight of 279.1. Cyclophosphamide is soluble in water, saline and ethanol.

Each capsule for oral administration contains 25 mg or 50 mg cyclophosphamide (anhydrous, USP) and the following inactive ingredients: pregelatinized starch and sodium stearyl fumarate.

Each gelatin capsule shell contains FD&C Blue #1, FD&C Red #40, gelatin and titanium dioxide.

In addition to the ingredients listed above, each capsule contains Opacode (Black) monogramming ink. Opacode (Black) contains ammonium hydroxide, iron oxide black, isopropyl alcohol, N-butyl alcohol, propylene glycol and shellac.

12 CLINICAL PHARMACOLOGY

12.1 Mechanism of Action

The mechanism of action is thought to involve cross-linking of tumor cell DNA.

12.2 Pharmacodynamics

Cyclophosphamide is biotransformed principally in the liver to active alkylating metabolites by a mixed function microsomal oxidase system. These metabolites interfere with the growth of susceptible rapidly proliferating malignant cells.

12.3 Pharmacokinetics

Following IV administration, elimination half-life (t½) ranges from 3 to 12 hours with total body clearance (CL) values of 4 to 5.6 L/h. Pharmacokinetics are linear over the dose range used clinically. When cyclophosphamide was administered at 4.0 g/m^2 over a 90 minutes infusion, saturable elimination in parallel with first-order renal elimination describe the kinetics of the drug.

Absorption

After oral administration, peak concentrations of cyclophosphamide occurred at one hour. Area under the curve ratio for the drug after oral and IV administration (AUCpo : AUCiv) ranged from 0.87 to 0.96.

Distribution

Approximately 20% of cyclophosphamide is protein bound, with no dose dependent changes. Some metabolites are protein bound to an extent greater than 60%. Volume of distribution approximates total body water (30 to 50 L).

Metabolism

The liver is the major site of cyclophosphamide activation. Approximately 75% of the administered dose of cyclophosphamide is activated by hepatic microsomal cytochrome P450s including CYP2A6, 2B6, 3A4, 3A5, 2C9, 2C18 and 2C19, with 2B6 displaying the highest 4-hydroxylase activity. Cyclophosphamide is activated to form 4-hydroxycyclophosphamide, which is in equilibrium with its ring-open tautomer aldophosphamide. 4-hydroxycyclophosphamide and aldophosphamide can undergo oxidation by aldehyde dehydrogenases to form the inactive metabolites 4-ketocyclophosphamide and carboxyphosphamide, respectively. Aldophosphamide can undergo β-elimination to form active metabolites phosphoramide mustard and acrolein. This spontaneous conversion can be catalyzed by albumin and other proteins. Less than 5% of cyclophosphamide may be directly detoxified by side chain oxidation, leading to the formation of inactive metabolites 2-dechloroethylcyclophosphamide. At high doses, the fraction of parent compound cleared by 4-hydroxylation is reduced resulting in non-linear elimination of cyclophosphamide in patients. Cyclophosphamide appears to induce its own metabolism. Auto-induction results in an increase in the total clearance, increased formation of 4-hydroxyl metabolites and shortened t½ values following repeated administration at 12- to 24-hour interval.

Elimination

Cyclophosphamide is primarily excreted as metabolites. 10 to 20% is excreted unchanged in the urine and 4% is excreted in the bile following IV administration.

Special Populations

Renal Impairment

The pharmacokinetics of cyclophosphamide were determined following one-hour intravenous infusion to renally impaired patients. The results demonstrated that the systemic exposure to cyclophosphamide increased as the renal function decreased. Mean dose-corrected AUC increased by 38% in the moderate renal group, (Creatinine clearance CrCl of 25 to 50 mL/min), by 64% in the severe renal group (CrCl of 10 to 24 mL/min) and by 23% in the hemodialysis group (CrCl of <10 mL/min) compared to the control group. The increase in exposure was significant in the severe group (p>0.05); thus, patients with severe renal impairment should be closely monitored for toxicity [see Use in Specific Populations (8.6)].

The dialyzability of cyclophosphamide was investigated in four patients on long-term hemodialysis. Dialysis clearance calculated by arterial-venous difference and actual drug recovery in dialysate averaged 104 mL/min, which is in the range of the metabolic clearance of 95 mL/min for the drug. A mean of 37% of the administered dose of cyclophosphamide was removed during hemodialysis. The elimination half-life (t½) was 3.3 hours in patients during hemodialysis, a 49% reduction of the 6.5 hours to t½ reported in uremic patients. Reduction in t½, larger dialysis clearance than metabolic clearance, high extraction efficiency, and significant drug removal during dialysis, suggest that cyclophosphamide is dialyzable.

Hepatic Impairment

Total body clearance (CL) of cyclophosphamide is decreased by 40% in patients with severe hepatic impairment and elimination half-life (t½) is prolonged by 64%. Mean CL and t½ were 45 ± 8.6 L/kg and 12.5 ± 1.0 hours respectively, in patients with severe hepatic impairment and 63 ± 7.6 L/kg and 7.6 ± 1.4 hours respectively in the control group [see Use in Specific Populations (8.7)].

13 NONCLINICAL TOXICOLOGY

13.1 Carcinogenesis, Mutagenesis, Impairment of Fertility

Cyclophosphamide administered by different routes, including intravenous, subcutaneous or intraperitoneal injection, or in drinking water, caused tumors in both mice and rats. In addition to leukemia and lymphoma, benign and malignant tumors were found at various tissue sites, including urinary bladder, mammary gland, lung, liver, and injection site [see Warnings and Precautions (5.5)].

Cyclophosphamide was mutagenic and clastogenic in multiple in vitro and in vivo genetic toxicology studies.

Cyclophosphamide is genotoxic in male and female germ cells. Animal data indicate that exposure of oocytes to cyclophosphamide during follicular development may result in a decreased rate of implantations and viable pregnancies, and in an increased risk of malformations. Male mice and rats treated with cyclophosphamide show alterations in male reproductive organs (e.g., decreased weights, atrophy, changes in spermatogenesis), and decreases in reproductive potential (e.g., decreased implantations and increased post-implantation loss) and increases in fetal malformations when mated with untreated females [see Use in Specific Populations (8.3)].

15 REFERENCES

1. OSHA Hazardous Drug. OSHA. http://www.osha.gov/SLTC/hazardousdrugs/index.html.

16 HOW SUPPLIED/STORAGE AND HANDLING

Cyclophosphamide Capsules, USP

25 mg, supplied as a blue/blue opaque capsule with “54 006” printed in black ink on the cap and body, containing a white to off-white powder.

NDC 0054-0382-13: Bottle of 30 Capsules

NDC 0054-0382-25: Bottle of 100 Capsules

50 mg, supplied as a blue/blue opaque capsule with “54 881” printed in black ink on the cap and body, containing a white to off-white powder.

NDC 0054-0383-13: Bottle of 30 Capsules

NDC 0054-0383-25: Bottle of 100 Capsules

Storage

Store at 20°C to 25°C (68°F to 77°F); with excursions permitted between 15ºC to 30ºC (59°F to 86°F). [See USP Controlled Room Temperature.]

Cyclophosphamide is an antineoplastic product. Follow special handling and disposal procedures.^1

17 PATIENT COUNSELING INFORMATION

Advise the patient of the following:

Myelosuppression, Immunosuppression, and Infections

- Inform patients of the possibility of myelosuppression, immunosuppression, and infections. Explain the need for routine blood cell counts. Instruct patients to monitor their temperature frequently and immediately report any occurrence of fever [see Warnings and Precautions (5.1)].

Urinary Tract and Renal Toxicity

- Advise the patient to report urinary symptoms (patients should report if their urine has turned a pink or red color) and the need for increasing fluid intake and frequent voiding [see Warnings and Precautions (5.2)].

Cardiotoxicity

- Advise patients to contact a health care professional immediately for any of the following: new onset or worsening shortness of breath, cough, swelling of the ankles/legs, palpitations, weight gain of more than 5 pounds in 24 hours, dizziness or loss of consciousness [see Warnings and Precautions (5.3)].

Pulmonary Toxicity

- Warn patients of the possibility of developing non-infectious pneumonitis. Advise patients to report promptly any new or worsening respiratory symptoms [see Warnings and Precautions (5.4)].

Embryo-Fetal Toxicity

- Inform female patients of the risk to a fetus and potential loss of the pregnancy. Advise females to inform their healthcare provider of a known or suspected pregnancy [see Warnings and Precautions (5.7) and Use in Specific Populations (8.1)].
- Advise females of reproductive potential to use effective contraception during treatment and for up to 1 year after completion of therapy [see Warnings and Precautions (5.7) and Use in Specific Populations (8.1, 8.3)]. Advise male patients with female partners of reproductive potential to use effective contraception during treatment and for 4 months after completion of therapy [see Warnings and Precautions (5.7) and Use in Specific Populations (8.1, 8.3)].

Lactation

- Advise lactating women not to breastfeed during treatment and for 1 week after the last dose of Cyclophosphamide Capsules [see Use in Specific Populations (8.2)].

Infertility

- Cyclophosphamide Capsules may impair fertility in males and females of reproductive potential [see Warnings and Precautions (5.8) and Use in Specific Populations (8.3, 8.4)].
  Common Adverse Reactions
- Explain to patients that side effects such as nausea, vomiting, stomatitis, impaired wound healing, amenorrhea, premature menopause, sterility and hair loss may be associated with cyclophosphamide administration. Other undesirable effects (including, e.g., dizziness, blurred vision, visual impairment) could affect the ability to drive or use machines [see Adverse Reactions (6.1, 6.2)].

Hydration and Important Administration Instructions

- Advise the patient that during or immediately after the administration, adequate amounts of fluid are required to reduce the risk of urinary tract toxicity [see Dosage And Administration (2.1)].
- Instruct the patient to swallow cyclophosphamide capsules whole. Do not open, chew, or crush capsules [see Dosage And Administration (2.1)].
- Advise caregivers to wear gloves when handling cyclophosphamide containers and capsules and to avoid exposure to broken capsules. If contact with broken capsules occurs, wash hands immediately and thoroughly [see Dosage And Administration (2.1)].

Distributed by: Hikma

Pharmaceuticals USA Inc.

Berkeley Heights, NJ 07922

C50000459/01

Revised July 2023